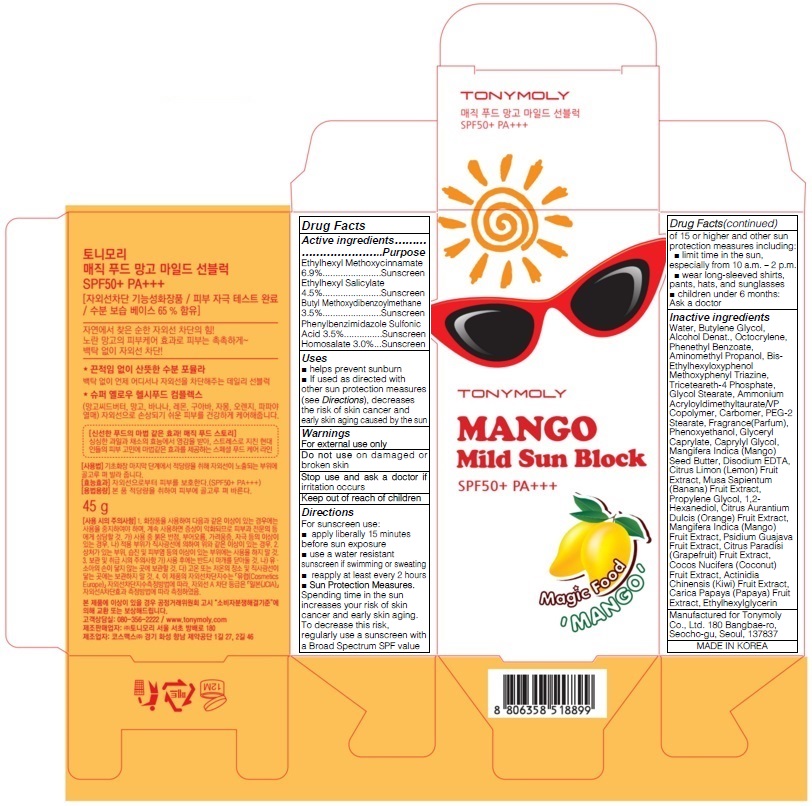 DRUG LABEL: TONYMOLY MAGIC FOOD MANGO MILD SUN BLOCK
NDC: 59078-210 | Form: CREAM
Manufacturer: TONYMOLY CO.,LTD
Category: otc | Type: HUMAN OTC DRUG LABEL
Date: 20160120

ACTIVE INGREDIENTS: OCTINOXATE 3.10 g/45 g; OCTISALATE 2.02 g/45 g; AVOBENZONE 1.57 g/45 g; ENSULIZOLE 1.57 g/45 g; HOMOSALATE 1.35 g/45 g
INACTIVE INGREDIENTS: Water; Butylene Glycol

ACTIVE INGREDIENT

Active ingredients: Ethylhexyl Methoxycinnamate 6.9%, Ethylhexyl Salicylate 4.5%, Butyl Methoxydibenzoylmethane 3.5%, Phenylbenzimidazole Sulfonic Acid 3.5%, Homosalate 3.0%

INACTIVE INGREDIENT

Inactive ingredients: Water, Butylene Glycol, Alcohol Denat., Octocrylene, Phenethyl Benzoate, Aminomethyl Propanol, Bis-Ethylhexyloxyphenol Methoxyphenyl Triazine, Triceteareth-4 Phosphate, Glycol Stearate, Ammonium Acryloyldimethyltaurate/VP Copolymer, Carbomer, PEG-2 Stearate, Fragrance(Parfum), Phenoxyethanol, Glyceryl Caprylate, Caprylyl Glycol, Mangifera Indica (Mango) Seed Butter, Disodium EDTA, Citrus Limon (Lemon) Fruit Extract, Musa Sapientum (Banana) Fruit Extract, Propylene Glycol, 1,2-Hexanediol, Citrus Aurantium Dulcis (Orange) Fruit Extract, Mangifera Indica (Mango) Fruit Extract, Psidium Guajava Fruit Extract, Citrus Paradisi (Grapefruit) Fruit Extract, Cocos Nucifera (Coconut) Fruit Extract, Actinidia Chinensis (Kiwi) Fruit Extract, Carica Papaya (Papaya) Fruit Extract, Ethylhexylglycerin

PURPOSE

Purpose: Sunscreen

WARNINGS

Warnings: For external use only

Do not use on damaged or broken skin

Stop use and ask a doctor if irritation occurs

Keep out of reach of children

DESCRIPTION

Uses: - helps prevent sunburn - If used as directed with other sun protection measures

Directions: decreases the risk of skin cancer and early skin aging caused by the sun

Directions:

For sunscreen use: - apply liberally 15 minutes before sun exposure - use a water resistant sunscreen if swimming or sweating - reapply at least every 2 hours - Sun Protection Measures. Spending time in the sun increases your risk of skin cancer and early skin aging. To decrease this risk, regularly use a sunscreen with a Broad Spectrum SPF value of 15 or higher and other sun protection measures including: - limit time in the sun, especially from 10 a.m. – 2 p.m. - wear long-sleeved shirts, pants, hats, and sunglasses - children under 6 months: Ask a doctor